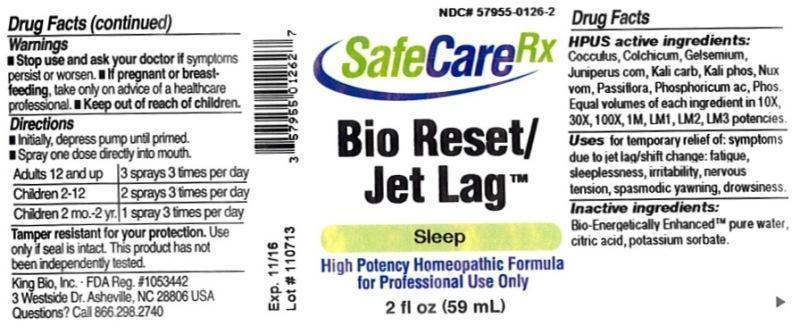 DRUG LABEL: Bio Reset/Jet Lag
NDC: 57955-0126 | Form: LIQUID
Manufacturer: King Bio Inc.
Category: homeopathic | Type: HUMAN OTC DRUG LABEL
Date: 20140417

ACTIVE INGREDIENTS: ANAMIRTA COCCULUS SEED 10 [hp_X]/59 mL; COLCHICUM AUTUMNALE BULB 10 [hp_X]/59 mL; GELSEMIUM SEMPERVIRENS ROOT 10 [hp_X]/59 mL; JUNIPER BERRY 10 [hp_X]/59 mL; POTASSIUM CARBONATE 10 [hp_X]/59 mL; POTASSIUM PHOSPHATE, DIBASIC 10 [hp_X]/59 mL; STRYCHNOS NUX-VOMICA SEED 10 [hp_X]/59 mL; PASSIFLORA INCARNATA FLOWERING TOP 10 [hp_X]/59 mL; PHOSPHORIC ACID 10 [hp_X]/59 mL; PHOSPHORUS 10 [hp_X]/59 mL
INACTIVE INGREDIENTS: WATER; CITRIC ACID MONOHYDRATE; POTASSIUM SORBATE

Bio Reset/Jet Lag™

ACTIVE INGREDIENT

Drug Facts__________________________________________________________________________________________________________

HPUS active ingredients: Cocculus indicus, Colchicum autumnale, Gelsemium sempervirens, Juniperus communis, Kali carbonicum, Kali phosphoricum, Nux vomica, Passiflora incarnata, Phosphoricum acidum, Phosphorus. Equal volumes of each ingredient in 10X, 30X, 100X,1M, LM1, LM2, LM3 potencies.

INDICATIONS AND USAGE

Uses for temporary relief of: symptoms due to jet lag/shift change: fatigue, sleeplessness, irritability, nervous tension, spasmodic yawning, drowsiness.

Inactive Ingredients:

Bio-Energetically Enhanced™ pure water, citric acid and potassium sorbate.

Warnings

- Stop use and ask your doctor if symptoms persist or worsen.
- If pregnant or breast-feeding, take only on advice of a healthcare professional.

- Keep out of reach of children.

Directions

- Initially, depress pump until primed.
- Spray one dose directly into mouth.
- Adults: 3 sprays 3 times per day.
- Children 2-12 years: 2 sprays 3 times per day.
- Use additionally as needed, up to 6 times per day.

OTHER SAFETY INFORMATION

Tamper resistant for your protection. Use only if safety seal is intact. This product has not been independently tested.

PURPOSE

Uses for temporary relief of: symptoms due to jet lag/shift change:

- fatigue
- sleeplessness
- irritability
- nervous tension
- spasmodic yawning
- drowsiness